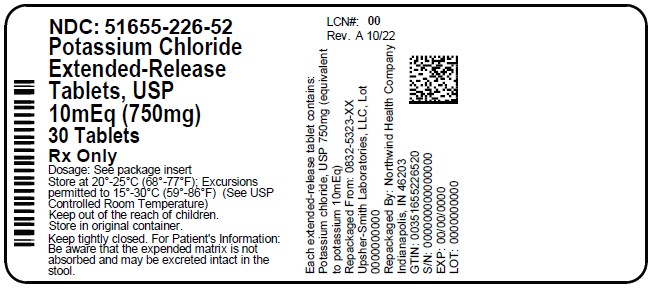 DRUG LABEL: Potassium Chloride
NDC: 51655-226 | Form: TABLET, FILM COATED, EXTENDED RELEASE
Manufacturer: Northwind Health Company, LLC
Category: prescription | Type: HUMAN PRESCRIPTION DRUG LABEL
Date: 20260101

ACTIVE INGREDIENTS: POTASSIUM CHLORIDE 750 mg/1 1
INACTIVE INGREDIENTS: HYDROGENATED COTTONSEED OIL; MAGNESIUM STEARATE; POLYETHYLENE GLYCOL, UNSPECIFIED; POLYVINYL ALCOHOL, UNSPECIFIED; SILICON DIOXIDE; TALC; TITANIUM DIOXIDE; D&C YELLOW NO. 10; FD&C YELLOW NO. 6

HIGHLIGHTS OF PRESCRIBING INFORMATION

These highlights do not include all the information needed to use POTASSIUM CHLORIDE EXTENDED-RELEASE safely and effectively. See full prescribing information for POTASSIUM CHLORIDE EXTENDED-RELEASE.
POTASSIUM CHLORIDE EXTENDED-RELEASE tablets, for oral use
Initial U.S. Approval: 1948

1 INDICATIONS AND USAGE

Potassium chloride extended-release is a potassium salt, indicated for the treatment and prophylaxis of hypokalemia with or without metabolic alkalosis in patients for whom dietary management with potassium-rich foods or diuretic dose reduction is insufficient. (1)

2 DOSAGE AND ADMINISTRATION

- Monitor serum potassium and adjust dosages accordingly. (2.1)
- If serum potassium is less than 2.5 mEq/L, use intravenous potassium instead of oral supplementation. (2.1)
- Take with meals and with a glass of water or other liquid. Swallow tablets whole without crushing, chewing or sucking. (2.1)
- Treatment of hypokalemia: Doses range from 40 to 100 mEq/day in divided doses. Limit doses to 40 mEq per dose. (2.2)
- Prevention of hypokalemia: Typical dose is 20 mEq per day. (2.2)

3 DOSAGE FORMS AND STRENGTHS

Tablets: 600 mg (8 mEq) and 750 mg (10 mEq) (3)

4 CONTRAINDICATIONS

- Concomitant use with triamterene and amiloride (4)

5 WARNINGS AND PRECAUTIONS

- Gastrointestinal Irritation: Take with meals. (5.1)

6 ADVERSE REACTIONS

- The most common adverse reactions are nausea, vomiting, flatulence, abdominal pain/discomfort and diarrhea. (6)

To report SUSPECTED ADVERSE REACTIONS, contact Upsher-Smith Laboratories, LLC at 1-855-899-9180 or FDA at 1-800-FDA-1088 or www.fda.gov/medwatch

7 DRUG INTERACTIONS

- Triamterene and amiloride: Concomitant use is contraindicated (7.1)
- Renin-angiotensin-aldosterone inhibitors: Monitor for hyperkalemia (7.2)
- Nonsteroidal anti-inflammatory drugs: Monitor for hyperkalemia (7.3)

8 USE IN SPECIFIC POPULATIONS

- Cirrhosis: Initiate therapy at the low end of the dosing range (8.6)
- Renal Impairment: Initiate therapy at the low end of the dosing range (8.7)

FULL PRESCRIBING INFORMATION

1 INDICATIONS AND USAGE

Potassium chloride extended-release is indicated for the treatment and prophylaxis of hypokalemia with or without metabolic alkalosis, in patients for whom dietary management with potassium-rich foods or diuretic dose reduction is insufficient.

2 DOSAGE AND ADMINISTRATION

2.1 Administration and Monitoring

If serum potassium concentration is less than 2.5 mEq/L, use intravenous potassium instead of oral supplementation.

Monitoring

Monitor serum potassium and adjust dosages accordingly. Monitor serum potassium periodically during maintenance therapy to ensure potassium remains in desired range.

The treatment of potassium depletion, particularly in the presence of cardiac disease, renal disease, or acidosis, requires careful attention to acid-base balance, volume status, electrolytes, including magnesium, sodium, chloride, phosphate, and calcium, electrocardiograms, and the clinical status of the patient. Correct volume status, acid-base balance, and electrolyte deficits as appropriate.

Administration

Take potassium chloride extended-release tablets with meals and with a glass of water or other liquid. Do not take potassium chloride extended-release tablets on an empty stomach because of its potential for gastric irritation [see Warnings and Precautions (5.1)] .

Swallow tablets whole without crushing, chewing or sucking.

2.2 Dosing

Dosage must be adjusted to the individual needs of each patient. Dosages greater than 40 mEq per day should be divided such that no more than 40 mEq is given in a single dose.

Treatment of Hypokalemia: Typical dose range is 40 to 100 mEq per day.

Maintenance or Prophylaxis: Typical dose range is 20 mEq per day.

3 DOSAGE FORMS AND STRENGTHS

Potassium chloride extended-release tablets are supplied as:

600 mg (8 mEq) are film-coated, round light blue tablets debossed with "KC 8".

750 mg (10 mEq) are film-coated, round yellow tablets debossed with "KC 10".

4 CONTRAINDICATIONS

Potassium chloride is contraindicated in patients on triamterene and amiloride.

5 WARNINGS AND PRECAUTIONS

5.1 Gastrointestinal Adverse Reactions

Solid oral dosage forms of potassium chloride can produce ulcerative and/or stenotic lesions of the gastrointestinal tract, particularly if the drug maintains contact with the gastrointestinal mucosa for prolonged periods. Consider the use of liquid potassium in patients with dysphagia, swallowing disorders, or severe gastrointestinal motility disorders.

If severe vomiting, abdominal pain, distention, or gastrointestinal bleeding occurs, discontinue potassium chloride extended-release tablets and consider possibility of ulceration, obstruction or perforation.

Potassium chloride extended-release tablets should not be taken on an empty stomach because of its potential for gastric irritation [see Dosage and Administration (2.1)] .

6 ADVERSE REACTIONS

The following adverse reactions have been identified with use of oral potassium salts. Because these reactions are reported voluntarily from a population of uncertain size, it is not always possible to reliably estimate their frequency or establish a causal relationship to drug exposure.

The most common adverse reactions to oral potassium salts are nausea, vomiting, flatulence, abdominal pain/discomfort, and diarrhea.

There have been reports hyperkalemia and of upper and lower gastrointestinal condition including obstruction, bleeding, ulceration, perforation.

Skin rash has been reported rarely.

7 DRUG INTERACTIONS

7.1 Triamterene or amiloride

Use with triamterene or amiloride can produce severe hyperkalemia. Concomitant use is contraindicated [see Contraindications (4)] .

7.2 Renin-angiotensin-aldosterone Inhibitors

Drugs that inhibit the renin-angiotensin-aldosterone system (RAAS) including angiotensin converting enzyme (ACE) inhibitors, angiotensin receptor blockers (ARBs), spironolactone, eplerenone, or aliskiren produce potassium retention by inhibiting aldosterone production. Closely monitor potassium in patients on concomitant RAAS inhibitors.

7.3 Nonsteroidal Anti-inflammatory Drugs (NSAIDs)

NSAIDs may produce potassium retention by reducing renal synthesis of prostaglandin E and impairing the renin-angiotensin system. Closely monitor potassium in patients on concomitant NSAIDs.

8 USE IN SPECIFIC POPULATIONS

8.1 Pregnancy

Risk Summary

There are no human data related to use of potassium chloride extended-release during pregnancy, and animal reproduction studies have not been conducted. Potassium supplementation that does not lead to hyperkalemia is not expected to cause fetal harm.

The background risk for major birth defects and miscarriage in the indicated population is unknown. All pregnancies have a background risk of birth defect, loss, or other adverse outcomes. In the U.S. general population, the estimated background risk of major birth defects and miscarriage in clinically recognized pregnancies is 2% to 4% and 15% to 20%, respectively.

8.2 Lactation

Risk Summary

The normal potassium ion content of human milk is about 13 mEq per liter. Since oral potassium becomes part of the body potassium pool, so long as body potassium is not excessive, the contribution of potassium chloride supplementation should have little or no effect on the level in human milk.

8.4 Pediatric Use

Safety and effectiveness in the pediatric population have not been established.

8.5 Geriatric Use

Clinical studies of potassium chloride extended-release did not include sufficient numbers of subjects aged 65 and over to determine whether they respond differently from younger subjects. Other reported clinical experience has not identified differences in responses between the elderly and younger patients. In general, dose selection for an elderly patient should be cautious, usually starting at the low end of the dosing range, reflecting the greater frequency of decreased hepatic, renal or cardiac function, and of concomitant disease or other drug therapy.

This drug is known to be substantially excreted by the kidney, and the risk of toxic reactions to this drug may be greater in patients with impaired renal function. Because elderly patients are more likely to have decreased renal function, care should be taken in dose selection, and it may be useful to monitor renal function.

8.6 Cirrhotics

Based on published literature, the baseline corrected serum concentrations of potassium measured over 3 hours after administration in cirrhotic subjects who received an oral potassium load rose to approximately twice that of normal subjects who received the same load. Patients with cirrhosis should usually be started at the low end of the dosing range, and the serum potassium level should be monitored frequently [see Clinical Pharmacology (12.3)] .

8.7 Renal Impairment

Patients with renal impairment have reduced urinary excretion of potassium and are at substantially increased risk of hyperkalemia. Patients with impaired renal function, particularly if the patient is on RAAS inhibitors or NSAIDs, should usually be started at the low end of the dosing range because of the potential for development of hyperkalemia [see Drug Interactions (7.2, 7.3)] . The serum potassium level should be monitored frequently. Renal function should be assessed periodically.

10 OVERDOSAGE

10.1 Symptoms

The administration of oral potassium salts to persons with normal excretory mechanisms for potassium rarely causes serious hyperkalemia. However, if excretory mechanisms are impaired, potentially fatal hyperkalemia can result [see Contraindications and Warnings] .

It is important to recognize that hyperkalemia is usually asymptomatic and may be manifested only by an increased serum potassium concentration (6.5 mEq/L to 8.0 mEq/L) and characteristic electrocardiographic changes (peaking of T-waves, loss of P-wave, depression of S-T segment and prolongation of the QT interval). Late manifestations include muscle paralysis and cardiovascular collapse from cardiac arrest (9 to 12 mEq/L).

10.2 Treatment

Treatment measures for hyperkalemia include the following:

- Elimination of foods and medications containing potassium and of any agents with potassium-sparing properties.
- Intravenous administration of 300 mL/hr to 500 mL/hr of 10% dextrose solution containing 10 to 20 units of crystalline insulin per 1,000 mL.
- Correction of acidosis, if present, with intravenous sodium bicarbonate.
- Use of exchange resins, hemodialysis or peritoneal dialysis.

In treating hyperkalemia, it should be recalled that in patients who have been stabilized on digitalis, too rapid a lowering of the serum potassium concentration can produce digitalis toxicity.

The extended-release feature means that absorption and toxic effects may be delayed for hours. Consider standard measures to remove any unabsorbed drug.

11 DESCRIPTION

Potassium chloride extended-release tablets, USP are a solid oral dosage form of potassium chloride. Each contains 600 mg or 750 mg of potassium chloride equivalent to 8 mEq or 10 mEq of potassium in a wax matrix tablet.

Potassium chloride extended-release tablets, USP, are an electrolyte replenisher. The chemical name is potassium chloride, and the structural formula is KCl. Potassium chloride, USP is a white, granular powder or colorless crystals. It is odorless and has a saline taste. Its solutions are neutral to litmus. It is freely soluble in water and insoluble in alcohol.

Inactive Ingredients: Hydrogenated vegetable oil, magnesium stearate, polyethylene glycol, polyvinyl alcohol, silicon dioxide, talc and titanium dioxide. Yellow tablets also contain D&C Yellow No. 10 Aluminum Lake and FD&C Yellow No. 6 Aluminum Lake. Blue tablets also contain FD&C Blue No. 1 Aluminum Lake and FD&C Blue No. 2 Aluminum Lake.

12 CLINICAL PHARMACOLOGY

12.1 Mechanism of Action

The potassium ion is the principal intracellular cation of most body tissues. Potassium ions participate in a number of essential physiological processes including the maintenance of intracellular tonicity, the transmission of nerve impulses, the contraction of cardiac, skeletal and smooth muscle and the maintenance of normal renal function.

The intracellular concentration of potassium is approximately 150 mEq to 160 mEq per liter. The normal adult plasma concentration is 3.5 mEq to 5 mEq per liter. An active ion transport system maintains this gradient across the plasma membrane.

Potassium is a normal dietary constituent and under steady state conditions the amount of potassium absorbed from the gastrointestinal tract is equal to the amount excreted in the urine. The usual dietary intake of potassium is 50 to 100 mEq per day.

12.3 Pharmacokinetics

The potassium chloride in potassium chloride extended-release is completely absorbed before it leaves the small intestine. The wax matrix is not absorbed and is excreted in the feces; in some instances the empty matrices may be noticeable in the stool. When the bioavailability of the potassium ion from the potassium chloride extended-release is compared to that of a true solution the extent of absorption is similar.

The extended-release properties of potassium chloride extended-release are demonstrated by the finding that a significant increase in time is required for renal excretion of the first 50% of the Potassium chloride extended-release dose as compared to the solution.

Increased urinary potassium excretion is first observed 1 hour after administration of potassium chloride extended-release, reaches a peak at approximately 4 hours, and extends up to 8 hours.

Mean daily steady-state plasma levels of potassium following daily administration of potassium chloride extended-release tablets cannot be distinguished from those following administration of potassium chloride solution or from control plasma levels of potassium ion.

Specific Populations

Cirrhotics

Based on published literature, the baseline corrected serum concentrations of potassium measured over 3 hours after administration in cirrhotic subjects who received an oral potassium load rose to approximately twice that of normal subjects who received the same load.

13 NONCLINICAL TOXICOLOGY

13.1 Carcinogenesis, Mutagenesis and Impairment of Fertility

Carcinogenicity, mutagenicity and fertility studies in animals have not been performed. Potassium is a normal dietary constituent.

16 HOW SUPPLIED/STORAGE AND HANDLING

Potassium chloride extended-release tablets, USP contains 750 mg of potassium chloride (equivalent to 10 mEq of potassium respectively).

Table 1: How Supplied
Dose | Shape | Color | Debossment | NDC#: 51655-xxx-xx
Dose | Shape | Color | Debossment | Bottle of 30 Tablets | Bottle of 90 Tablets
750 mg (10 mEq) | round | yellow | "KC 10" | 226-52 | 226-26

STORAGE AND HANDLING

Store at 20° to 25°C (68° to 77°F); excursions permitted to 15° to 30°C (59° to 86°F) [See USP Controlled Room Temperature].

Dispense in a tight container with a child-resistant closure.

Keep tightly closed.

17 PATIENT COUNSELING INFORMATION

- Inform patients to take each dose with meals and with a full glass of water or other liquid, and to not crush, chew, or suck the tablets. Inform patients that the wax matrix is not absorbed and is excreted in the feces; in some instances, the empty matrices may be noticeable in the stool.
- Advise patients seek medical attention if tarry stools or other evidence of gastrointestinal bleeding is noticed.

Manufactured by
UPSHER-SMITH LABORATORIES, LLC
Maple Grove, MN 55369

Revised: 12/2020

Principal Display Panel

NDC: 51655-226-52